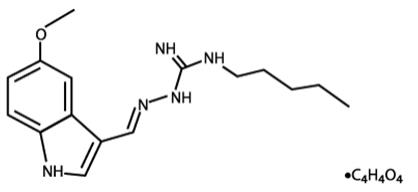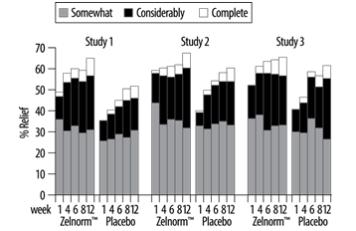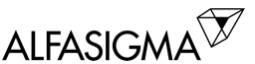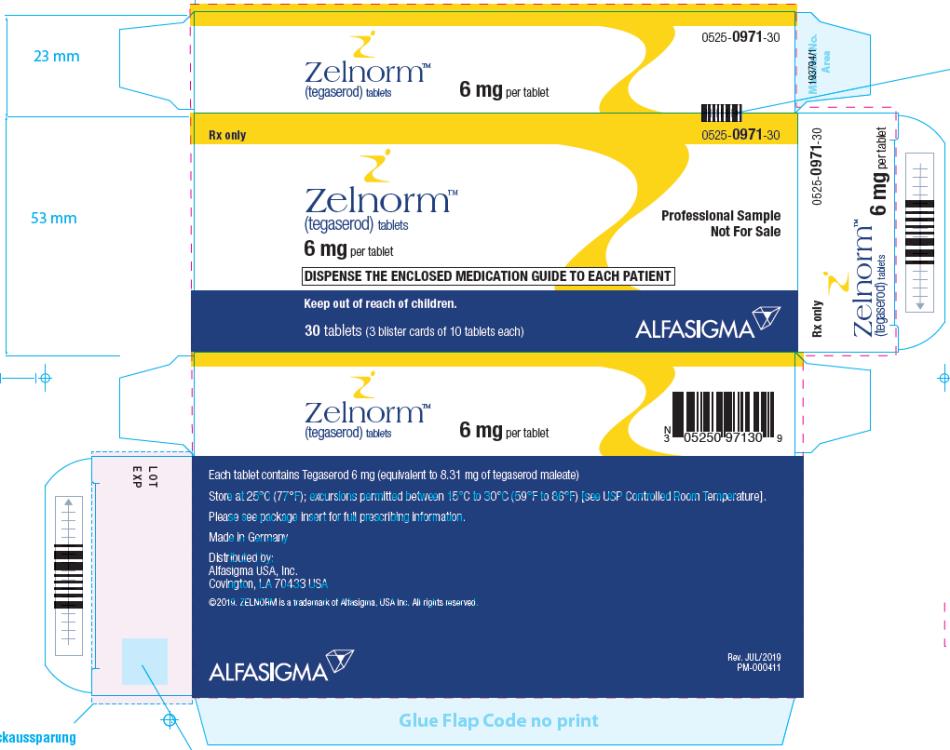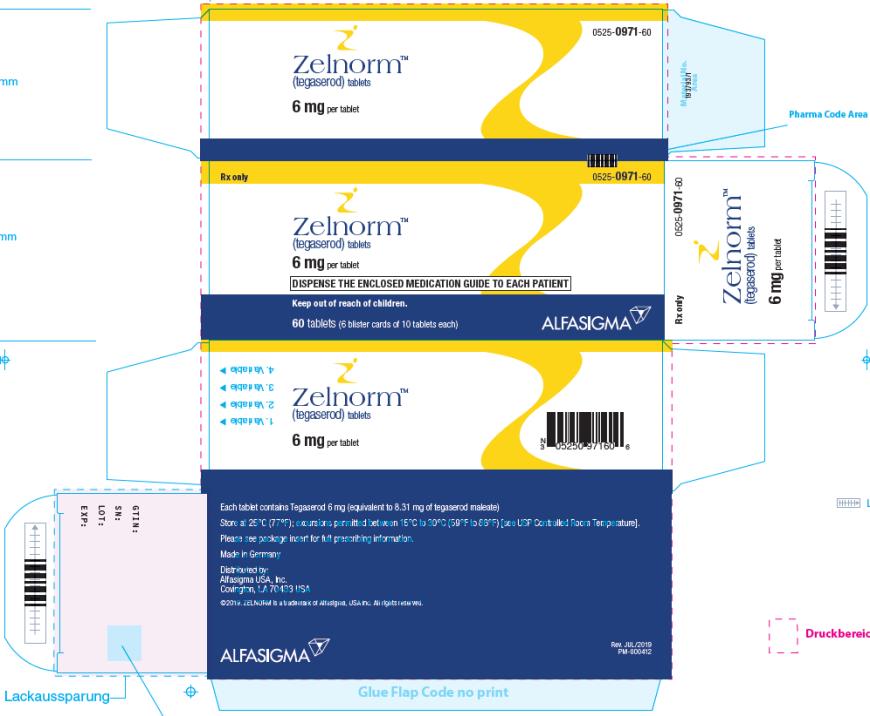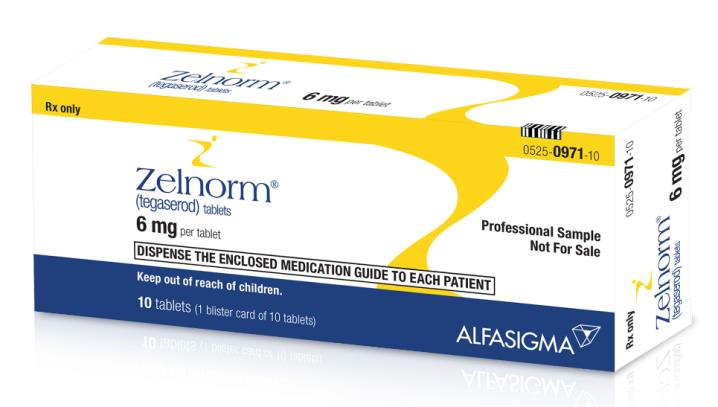 DRUG LABEL: ZELNORM
NDC: 0525-0971 | Form: TABLET
Manufacturer: Alfasigma USA, Inc.
Category: prescription | Type: HUMAN PRESCRIPTION DRUG LABEL
Date: 20200609

ACTIVE INGREDIENTS: TEGASEROD 6 mg/1 1
INACTIVE INGREDIENTS: SILICON DIOXIDE; CROSPOVIDONE; GLYCERYL DIBEHENATE; LACTOSE MONOHYDRATE; HYPROMELLOSES

HIGHLIGHTS OF PRESCRIBING INFORMATION

These highlights do not include all the information needed to use ZELNORM™ safely and effectively. See full prescribing information for ZELNORM™.
ZELNORM™ (tegaserod) tablets, for oral use
Initial U.S. Approval: 2002

RECENT MAJOR CHANGES

Indications and Usage (1) | 03/2019
Contraindications (4) | 03/2019
Warnings and Precautions (6) | 03/2019

1 INDICATIONS AND USAGE

ZELNORM is a serotonin-4 (5-HT4) receptor agonist indicated for the treatment of adult women less than 65 years of age with irritable bowel syndrome with constipation (IBS-C). (1)

Limitations of Use:

- The safety and effectiveness of ZELNORM in men with IBS-C have not been established. (1)

2 DOSAGE AND ADMINISTRATION

The recommended dosage in adult women less than 65 years of age is 6 mg taken twice daily orally at least 30 minutes before meals. Discontinue ZELNORM in patients who have not had adequate control of symptoms after 4 to 6 weeks of treatment. (2)

3 DOSAGE FORMS AND STRENGTHS

Tablets: 6 mg tegaserod. (3)

4 CONTRAINDICATIONS

ZELNORM is contraindicated in patients with:

- A history of myocardial infarction, stroke, transient ischemic attack, or angina. (4, 5.1)
- A history of ischemic colitis or other forms of intestinal ischemia. (4, 5.2)
- Severe renal impairment (eGFR< 15 mL/min/1.73 m2) or end-stage renal disease. (4, 8.6)
- Moderate or severe hepatic impairment (Child-Pugh B or C). (4, 8.7)
- A history of bowel obstruction, symptomatic gallbladder disease, suspected sphincter of Oddi dysfunction, or abdominal adhesions. (4)
- Hypersensitivity to tegaserod. (4)

5 WARNINGS AND PRECAUTIONS

- Cardiovascular Ischemic Events, Including Major Adverse Cardiovascular Events (MACE): The potential risks of treatment must be balanced with expectations in improvements in symptoms of IBS-C. Discontinue ZELNORM treatment in patients who experience a myocardial infarction, stroke, transient ischemic attack or angina. (4) Evaluate the risks and benefits of continued treatment in patients who develop clinical or other evidence of cardiovascular ischemic heart disease and/or experience changes in health status that could increase cardiovascular risk during treatment. (4, 5.1)
- Ischemic Colitis: Monitor for rectal bleeding, bloody diarrhea, and new or worsening abdominal pain and discontinue ZELNORM if symptoms develop. (5.2)
- Volume Depletion Associated with Diarrhea: Avoid use in patients with severe diarrhea. Instruct patients to discontinue ZELNORM and contact their healthcare provider if severe diarrhea, hypotension or syncope occur. (5.3)
- Suicidal Ideation and Behavior: Monitor patients for clinical worsening of depression and emergence of suicidal thoughts and behaviors, especially during the initial few months of treatment. Instruct patients to immediately discontinue ZELNORM and contact their healthcare provider if their depression is persistently worse or they are experiencing emergent suicidal thoughts or behaviors. (5.4)

6 ADVERSE REACTIONS

Most common adverse reactions (>2%) are headache, abdominal pain, nausea, diarrhea, flatulence, dyspepsia, and dizziness. (6.1)

To report SUSPECTED ADVERSE REACTIONS, contact Alfasigma USA at 1-855-697-9232 or FDA at 1-800-FDA-1088 or www.fda.gov/medwatch.

8 USE IN SPECIFIC POPULATIONS

Lactation: Breastfeeding not recommended. (8.2)

FULL PRESCRIBING INFORMATION

1 INDICATIONS AND USAGE

ZELNORM is indicated for the treatment of adult women less than 65 years of age with irritable bowel syndrome with constipation (IBS-C).

Limitations of Use

- The safety and effectiveness of ZELNORM in men with IBS-C have not been established [see Clinical Studies (14)].

2 DOSAGE AND ADMINISTRATION

The recommended dosage of ZELNORM in adult women less than 65 years of age is 6 mg taken twice daily orally at least 30 minutes before meals [see Clinical Pharmacology (12.3)]. Discontinue ZELNORM in patients who have not had adequate control of symptoms after 4 to 6 weeks of treatment.

3 DOSAGE FORMS AND STRENGTHS

ZELNORM Tablets: 6 mg tegaserod; supplied as whitish to slightly yellowish, round flat tablet with a beveled edge engraved with “ZEL” and “6”.

4 CONTRAINDICATIONS

ZELNORM is contraindicated in patients with:

- A history of myocardial infarction (MI), stroke, transient ischemic attack (TIA), or angina [see Warnings and Precautions (5.1)]
- A history of ischemic colitis or other forms of intestinal ischemia [see Warnings and Precautions (5.2)]
- Severe renal impairment (eGFR< 15 mL/min/1.73 m^2) or end-stage renal disease [see Use in Specific Populations (8.6)]
- Moderate and severe hepatic impairment (Child-Pugh B or C) [see Use in Specific Populations (8.7)]
- A history of bowel obstruction, symptomatic gallbladder disease, suspected sphincter of Oddi dysfunction, or abdominal adhesions [see Adverse Reactions (6.2)]
- Hypersensitivity to tegaserod [see Adverse Reactions (6.2)]

5 WARNINGS AND PRECAUTIONS

5.1 Cardiovascular Ischemic Events, Including Major Adverse Cardiovascular Events (MACE)

Stroke, MI, and cardiovascular death (major adverse cardiovascular events [MACE]) have been reported in adults taking ZELNORM who had an increased risk of developing an adverse cardiovascular event based on their medical history [see Adverse Reactions (6.1)].

ZELNORM is contraindicated in patients with a history of MI, stroke, TIA, or angina [see Contraindications (4)]. Assess female patients less than 65 years of age for a history of cardiovascular disease and cardiovascular risk factors prior to treatment with ZELNORM [see Adverse Reactions (6.1)]. The potential risks of treatment must be balanced with expectations in improvements in symptoms of IBS-C.

Discontinue ZELNORM in patients who experience an MI, stroke, TIA, or angina [see Contraindications (4)]. Evaluate the risks and benefits of continued use of ZELNORM in patients who develop clinical or other evidence of cardiovascular ischemic heart disease (e.g., coronary artery disease) and/or experience changes in health status that could increase cardiovascular risk during treatment with ZELNORM.

5.2 Ischemic Colitis

Ischemic colitis and other forms of intestinal ischemia have been reported postmarketing in patients receiving ZELNORM [see Adverse Reactions (6.2)]. In some cases, hospitalization was required. Discontinue ZELNORM in patients who develop symptoms of ischemic colitis, such as rectal bleeding, bloody diarrhea, or new or worsening abdominal pain. Evaluate patients experiencing these symptoms promptly and perform appropriate diagnostic testing. Do not reinitiate ZELNORM in patients who develop findings consistent with ischemic colitis or other forms of intestinal ischemia [see Contraindications (4)].

5.3 Volume Depletion Associated with Diarrhea

Diarrhea is one of the most common adverse reactions in ZELNORM-treated patients from the pooled IBS-C double-blind, placebo-controlled trials. Diarrhea resulted in discontinuation in 1.6% of ZELNORM-treated patients compared to 0% in placebo [see Adverse Reactions (6)].

In postmarketing experience, serious consequences of diarrhea including hypovolemia, hypotension, and syncope have been reported in patients treated with ZELNORM. In some cases, these complications have required hospitalization for rehydration. Avoid use of ZELNORM in patients who are currently experiencing or frequently experience diarrhea. Instruct patients to discontinue ZELNORM and contact their healthcare provider if severe diarrhea, hypotension, or syncope occur.

5.4 Suicidal Ideation and Behavior

Suicide, suicidal attempt and ideation, and self-injurious behavior have been reported in clinical trials of IBS-C and other gastrointestinal motility disorders.The frequency of suicidal ideation or attempts with tegaserod treatment (8 patients out of 10,003) was higher than placebo (1 patient out of 5,425) [see Adverse Reactions (6.1)]. Suicidal ideation/behavior in clinical trials was proportionately more frequent among patients receiving antidepressant medication.

Monitor all ZELNORM-treated patients for clinical worsening of depression and emergence of suicidal thoughts and behaviors, especially during the initial few months of treatment. Counsel family members and caregivers of patients to monitor for changes in behavior and to alert the healthcare provider. Instruct patients to immediately discontinue ZELNORM and contact their healthcare provider if their depression is persistently worse or they are experiencing emergent suicidal thoughts or behaviors.

6 ADVERSE REACTIONS

The following adverse reactions are discussed in more detail elsewhere in the labeling:

- Cardiovascular Ischemic Events, including MACE [see Warnings and Precautions (5.1)]
- Ischemic Colitis [see Warnings and Precautions (5.2)]
- Volume Depletion Associated with Diarrhea [see Warnings and Precautions (5.3)]
- Suicidal Ideation and Behavior [see Warnings and Precautions (5.4)]

6.1 Clinical Trials Experience

Because clinical trials are conducted under widely varying conditions, adverse reaction rates observed in the clinical trials of a drug cannot be directly compared to rates in the clinical trials of another drug and may not reflect the rates observed in practice.

Common Adverse Reactions

In three clinical trials 2,343 female patients less than 65 years of age with IBS-C received ZELNORM 6 mg twice daily or placebo. The majority of patients were Caucasian. Table 1 provides the incidence of common adverse reactions reported in >2% of IBS-C patients in the ZELNORM treatment group and at an incidence that was greater than in the placebo group.

Table 1. Most Common Adverse Reactionsa in Three Placebo-Controlled Trials of ZELNORM in Female IBS-C Patients Less than 65 Years of Age
Adverse Reactions | ZELNORM 6 mg twice daily [N = 1,184] % | Placebo [N = 1,159] %
Headache | 14 | 10
Abdominal Painb | 11 | 10
Nausea | 8 | 7
Diarrhea | 8 | 3
Flatulence | 6 | 5
Dyspepsia | 4 | 3
Dizziness | 4 | 3
a Reported in >2% of ZELNORM-treated patients and at an incidence greater than placebo
b Includes abdominal pain, upper abdominal pain, lower abdominal pain, abdominal discomfort, abdominal tenderness, epigastric pain or discomfort

Diarrhea

The majority (84%) of the ZELNORM patients reporting diarrhea had a single episode. In most cases, diarrhea occurred within the first week of treatment. Typically, diarrhea resolved with continued therapy. Diarrhea resulted in discontinuation in 1.6% of ZELNORM-treated patients compared to 0% in placebo [see Warnings and Precautions (5.3)].

Less Common Adverse Reactions

The following is a list of less common adverse reactions reported in ≤ 2% of patients in clinical trials of IBS-C on ZELNORM but more frequently than placebo:

Blood and Lymphatic System Disorders: Anemia

Ear and Labyrinth Disorders: Vertigo

Gastrointestinal Disorders: Rectal hemorrhage

General Disorders and Administration Site Conditions: Asthenia

Investigations: Increased blood creatine phosphokinase

Metabolism and Nutrition Disorders: Increased appetite

Musculoskeletal and Connective Tissue Disorders: Arthropathy, tendonitis

Nervous System Disorders: Migraine

Adverse Reactions of Special Interest

ZELNORM is recommended for use in female patients with IBS-C, and is not recommended for other motility disorders [see Indications and Dosage (1)].

Major Adverse Cardiovascular Events (MACE)

A retrospective analysis of the pooled clinical trial database data (involving 18,645 patients, both male and female) of 29 placebo-controlled trials of IBS-C and other gastrointestinal motility disorders of at least four weeks duration was conducted. An external adjudication of the reported cardiovascular ischemic (CVI) events identified an imbalance in patients taking ZELNORM (13 events, 0.1%) compared to placebo (1 event, 0.01%). A second external adjudication was conducted with additional patient-level information, and used a comprehensive pre-specified methodology regarding both case selection and assessment. This adjudication confirmed seven CVI events (0.06%) on ZELNORM compared to one event (0.01%) on placebo. An imbalance in MACE events (defined as cardiovascular death, non-fatal MI, non-fatal stroke) was observed in patients taking ZELNORM compared to placebo, as reported in both external adjudications. All events occurred in male and female patients with a history of cardiovascular ischemic disease and/or more than one cardiovascular risk factor.

A summary of the event rates from both adjudications is provided in Table 2. The rate of MACE events for ZELNORM-treated patients ranged from 0.03% to 0.06% in the overall population and 0.01% to 0.03% in the female population less than 65 years of age without a history of cardiovascular ischemic disease compared to zero in the placebo-treated group.

Table 2. Number of MACE Events Confirmed in Two External Adjudications of the Clinical Trial Database
 | All Patients (Male and Female) |  | Females < 65 Years of Age
 |  |  | Without a History of Cardiovascular Ischemic Diseasea |  | Without a History of Cardiovascular Ischemic Diseasea and One or Fewer Cardiovascular Risk Factorsb
 | ZELNORM (N=11,614) | Placebo (N=7,031) | ZELNORM (N=9,547) | Placebo (N=5,748) | ZELNORM (N=7,785) | Placebo (N=4,686)
 | n (%) | n (%) | n (%) | n (%) | n (%) | n (%)
First External Adjudication | 7c | 0 | 3e | 0 | 0 | 0
 | 0.06% |  | 0.03%
Second External Adjudication | 4d | 0 | 1f | 0 | 0 | 0
 | 0.03% |  | 0.01%
a Defined as prior MI, stroke, transient ischemic attack, angina, etc.
b Defined as active smoking, current hypertension/history of antihypertensive treatment, current hyperlipidemia/history of lipid lowering medication, history of diabetes mellitus, age ≥55 years, or obesity (BMI >30 kg/m^2)
c Five females less than 65 years, one male less than 65 years and one male greater than 65 years of age
d Three females less than 65 years of age and one male greater than 65 years of age
e Cardiovascular death, MI and stroke; all three patients had > one cardiovascular risk factor at baseline
f Cardiovascular death (one of the three cases confirmed in the 1st external adjudication)

Suicidal Ideation/Behavior

Two ZELNORM-treated patients committed suicide, one in a controlled study of IBS-C and one during open label treatment for another motility disorder. In 27 placebo-controlled trials, assessing tegaserod at a total daily dose of 4 mg to 50 mg (up to four times the recommended daily dose), or placebo for the treatment of IBS-C or other gastrointestinal motility disorders, the frequency of suicidal ideation/behavior with tegaserod treatment (8 events/10,003, or 0.08%) was higher than placebo (1 event/5,425, or 0.02%). Events on ZELNORM included one completed suicide, two suicide attempts, four cases of self-injurious behavior, and one case of suicidal ideation. There was one suicide attempt on placebo. Of the eight ZELNORM-treated patients who experienced an event, all were less than 65 years of age, seven were female and three had IBS-C. The patient who committed suicide was a female, less than 65 years of age with IBS-C, taking ZELNORM 2 mg twice daily.

Abdominal Surgeries, Including Cholecystectomy

An increase in abdominal surgeries was observed on ZELNORM (9 patients out of 2,965 or 0.3%) versus placebo (3 patients out of 1,740 or 0.2%) in clinical trials of men and women treated with ZELNORM for IBS-C. The increase was primarily due to a numerical imbalance in cholecystectomies reported in patients treated with ZELNORM (5 patients out of 2,965 or 0.17%) versus placebo (1 patient out of 1,740 or 0.06%). A causal relationship between abdominal surgeries and ZELNORM has not been established.

6.2 Postmarketing Experience

The following adverse reactions have been identified during postapproval use of ZELNORM. Because these reactions are reported voluntarily from a population of uncertain size, it is not always possible to reliably estimate their frequency or establish a causal relationship to drug exposure.

- Ischemic colitis, mesenteric ischemia, gangrenous bowel and rectal bleeding [see Warnings and Precautions (5.2)]
- Severe diarrhea resulting in syncope, hypotension, hypovolemia, electrolyte disorders [see Warnings and Precautions (5.3)]
- Sphincter of Oddi spasm, bile duct stone, cholecystitis with elevated transaminases, elevation in ALT, AST and bilirubin, hepatitis [see Contraindications (4)]
- Alopecia
- Hypersensitivity reactions, including anaphylaxis [see Contraindications (4)]

8 USE IN SPECIFIC POPULATIONS

8.1 Pregnancy

Risk Summary

Available data from case reports with ZELNORM use in pregnant women have not identified a drug-associated risk of major birth defects, miscarriage, or adverse maternal or fetal outcomes. In animal reproduction studies, decreased survival of rat pups was observed with maternal dietary administration of tegaserod at 71 times the recommended dose during organogenesis and through lactation. Decreased body weight and delays in developmental landmarks in rat pups were observed with maternal dietary administration of 45 times the recommended dose (see Data).

The estimated background risk of major birth defects and miscarriage for the indicated population is unknown. All pregnancies have a background risk of birth defect, loss, or other adverse outcomes. In the U.S. general population, the estimated background risk of major birth defects and miscarriage in clinically recognized pregnancies is 2% to 4% and 15% to 20%, respectively.

Data

Animal Data

No adverse developmental effects were observed with oral administration of tegaserod to pregnant rats at doses up to 100 mg/kg/day (approximately 15 times the recommended dose based on area under the plasma concentration-time curve [AUC]) or to pregnant rabbits at doses up to 120 mg/kg/day (approximately 51 times the recommended dose based on AUC) during organogenesis.

A pre- and postnatal developmental toxicity study was performed in rats using dietary administration of up to 300 mg/kg/day (71 times the recommended dose based on AUC) during organogenesis and through lactation. The survival rate through postnatal days 4 and 21 was 59% at 300 mg/kg/day as compared to 95% to 99% in the control group. At doses of 150 mg/kg/day and higher (45 times the recommended dose based on AUC), decreased body weight and delays in developmental landmarks were observed. No adverse effects were observed at 75 mg/kg/day (14 times the recommended dose based on AUC).

8.2 Lactation

Risk Summary

There are no data regarding the presence of tegaserod in human milk, the effects on the breastfed infant, or the effects on milk production. Tegaserod and its metabolites are present in rat milk; the milk to plasma concentration ratio for tegaserod is very high (see Data). When a drug is present in animal milk, it is likely that the drug will be present in human milk. Because of the potential for serious reactions in the breastfed infant, including tumorigenicity [see Nonclinical Toxicology (13.1)], advise a lactating woman that breastfeeding is not recommended during treatment with ZELNORM.

Data

Following oral administration, tegaserod and its metabolites are excreted in the milk of lactating rats with a milk to plasma concentration ratio of 33:1 at eight hours.

8.4 Pediatric Use

Safety and effectiveness of ZELNORM in pediatric patients have not been established.

8.5 Geriatric Use

ZELNORM is not indicated in patients 65 years of age and older.

8.6 Renal Impairment

ZELNORM is contraindicated in patients with severe renal impairment (eGFR < 15 mL/min/1.73 m^2) or end stage renal disease [see Contraindications (4)]. The Cmax and AUC of the tegaserod metabolite, 5-methoxyindole-3-carboxylic acid glucuronide (M29), are substantially increased in severe renal impairment [see Clinical Pharmacology (12.3)].

No dosage adjustment is recommended in patients with mild to moderate renal impairment (eGFR ≥ 30 mL/min/1.73 m^2).

8.7 Hepatic Impairment

ZELNORM is contraindicated in patients with moderate or severe hepatic impairment (Child-Pugh B or C) [see Contraindications (4)].

No dosage adjustment is necessary in patients with mild hepatic impairment [see Clinical Pharmacology (12.3)].

10 OVERDOSAGE

Single oral doses of 120 mg (20 times the recommended dose) of ZELNORM were administered to three healthy subjects in one study. All three subjects developed diarrhea and headache. Two of these subjects also reported intermittent abdominal pain and one developed orthostatic hypotension. In 28 healthy subjects exposed to 90 to 180 mg per day of ZELNORM (7.5 to 15 times the recommended daily dosage) for several days, adverse reactions were diarrhea (100%), headache (57%), abdominal pain (18%), flatulence (18%), nausea (7%), and vomiting (7%).

Based on the large distribution volume and high protein binding of tegaserod, it is unlikely that tegaserod could be removed by dialysis. In cases of overdosage, treat symptomatically and institute supportive measures as appropriate.

11 DESCRIPTION

ZELNORM oral tablets contain tegaserod, a serotonin-4 (5-HT4) receptor agonist, as the hydrogen maleate salt. As the maleate salt, tegaserod is chemically designated as 3-(5-methoxy-1H-indol-3-ylmethylene)-N-pentylcarbazimidamide hydrogen maleate. Its empirical formula is C16H23N5O•C4H4O4. The molecular weight is 417.47 and the structural formula is:

Tegaserod as the maleate salt is a white to off-white crystalline powder and is slightly soluble in ethanol and very slightly soluble in water. Each ZELNORM tablet contains 6 mg of tegaserod (equivalent to 8.31 mg of tegaserod maleate) and the following inactive ingredients: colloidal silicon dioxide, crospovidone, glyceryl behenate, hypromellose, and lactose monohydrate.

12 CLINICAL PHARMACOLOGY

12.1 Mechanism of Action

Tegaserod is an agonist of serotonin type-4 (5-HT4) receptors that stimulates the peristaltic reflex and intestinal secretion, inhibits visceral sensitivity, enhances basal motor activity, and normalizes impaired motility throughout the gastrointestinal tract.

Based on in vitro binding affinity and functional assessment, at clinically relevant plasma concentrations, tegaserod is an antagonist at 5-HT2B receptors in humans. It is expected to have minimal binding to 5-HT1 receptors. Tegaserod has no affinity for 5-HT3 or dopamine receptors.

The main metabolite, M29, has negligible affinity for 5-HT4 receptors in vitro.

In vivo studies showed that tegaserod enhanced basal motor activity and normalized impaired motility throughout the gastrointestinal tract. In addition, studies demonstrated that tegaserod moderated visceral sensitivity during colorectal distension in animals.

12.2 Pharmacodynamics

Cardiac Electrophysiology

Centrally analyzed ECGs were recorded in 4,605 male and female patients receiving ZELNORM 6 mg twice daily or placebo for IBS-C and other related motility disorders. No subject receiving tegaserod had an absolute QTcF above 480 ms. An increase in QTcF of 30 to 60 ms was observed in 7% of patients receiving ZELNORM and 8% receiving placebo. An increase in QTcF of greater than 60 ms was observed in 0.3% and 0.2% of subjects, respectively. The effects of tegaserod on the QTcF interval were not considered to be clinically meaningful.

Platelet Aggregation

There is a potential for tegaserod and its main metabolite (M29) to increase platelet aggregation in vitro. In one in vitro study, tegaserod, at concentrations up to 10 times the maximum plasma concentration (Cmax) at the recommended dose, significantly increased platelet aggregation in a concentration-dependent manner up to 74% (range 11% to 74%) compared to vehicle control (with potentiation by various agonists). In another in vitro study, M29, at concentrations up to 0.6 times the Cmax of M29 also showed a 5% to 16% increase in platelet aggregation compared to vehicle control. The clinical implications of the in vitro platelet aggregation results are unclear.

12.3 Pharmacokinetics

The pharmacokinetics of tegaserod in IBS-C patients are comparable to those in healthy subjects. The mean (±SD) peak tegaserod concentration (Cmax) was 2.9 (±1.1) ng/mL, and mean (±SD) AUC was 10.5 (±4.6) h•ng/mL following a single ZELNORM dose at 6 mg. Tegaserod systemic exposure at steady state increase proportionally over a dose range of 2 mg to 12 mg twice daily (0.3 to 2 times the approved recommended dosage). There was no significant accumulation (~10%) of tegaserod following the approved recommended dosage.

Absorption

The absolute bioavailability of tegaserod is approximately 10% when administered to fasting subjects. The median time to peak tegaserod plasma concentration (Tmax) is approximately one hour (range 0.7 to 2 hours).

Effect of Food

Compared to under fasted conditions, the tegaserod AUC was reduced by 40% to 65%, Cmax was reduced by approximately 20% to 40% and median Tmax was 0.7 hours when ZELNORM was administered 30 minutes before a high-fat, high-calorie meal (approximately 150 calories from protein, 250 calories from carbohydrates, and 500 calories from fat). Plasma concentrations were similar when ZELNORM was administered within 30 minutes prior to a meal or 2.5 hours after a meal [see Dosage and Administration (2)].

Distribution

Protein binding of tegaserod is approximately 98%. The mean volume of distribution of tegaserod (± SD) at steady-state is 368 ± 223 L following intravenous administration (ZELNORM is not approved for intravenous administration).

Elimination

The mean tegaserod terminal elimination half-life ranged from 4.6 to 8.1 hours following oral administration and the mean (± SD) plasma clearance was 77 ± 15 L/h following intravenous administration.

Metabolism

Tegaserod is metabolized via hydrolysis and direct glucuronidation. Tegaserod undergoes hydrolysis in the stomach followed by oxidation and conjugation which produces the M29 metabolite.

Excretion

Approximately two-thirds of a ZELNORM dose is excreted unchanged in the feces, with the remaining one-third excreted in the urine as metabolites.

Specific Populations

Patients with Renal Impairment

No change in the pharmacokinetics of tegaserod was observed in subjects with end stage renal disease (creatinine clearance normalized by body surface area (CrCL) < 15 mL/min/1.73 m^2) requiring hemodialysis. Although renal impairment does not affect the pharmacokinetics of tegaserod, the pharmacokinetics of its main metabolite (M29) are altered, the Cmax of M29 doubling and the AUC increasing 10-fold in patients with severe renal impairment (CrCL < 15 mL/min/1.73 m^2) compared to healthy subjects with normal renal function (CrCL > 80 mL/min/1.73 m^2) [see Contraindications (4), Use in Specific Populations (8.6)].

Patients with Hepatic Impairment

In subjects with mild hepatic impairment (Child-Pugh A), the mean tegaserod AUC was 31% higher and the Cmax was 16% higher compared to healthy subjects with normal hepatic function. The increase in exposure in subjects with mild impairment is not considered to be clinically relevant.

In a single subject with moderate hepatic impairment, the Cmax and AUC were 140% and 200% of that observed in healthy controls. ZELNORM has not been studied in patients with moderate or severe hepatic impairment (Child-Pugh B or C) [see Contraindications (4), Use in Specific Populations (8.7)].

Drug Interaction Studies

Effect of Other Drugs on Tegaserod

Quinidine: Coadministration of a single dose of 600 mg quinidine (P-gp inhibitor) with a single dose of ZELNORM 6 mg increased the mean tegaserod AUC(0-12h) and the mean Cmax by 50% and 44%, respectively, compared to ZELNORM administered alone. Coadministration of multiple doses of quinidine (600 mg once daily for three days) with ZELNORM 6 mg twice daily for six days increased the mean tegaserod AUC(0-12h) and Cmax by 71% and 63%, respectively, compared to ZELNORM administered alone.

Inhibitors of P-gp (e.g., ritonavir, clarithromycin, itraconazole) may modestly increase the oral bioavailability of tegaserod. The clinical relevance of increased systemic exposure as a result of P-gp inhibition is unclear.

Omeprazole: Administration of omeprazole 20 mg once daily for four days followed by ZELNORM 6 mg twice daily on day four increased the mean tegaserod AUC and Cmax by 15% and 17%, respectively, compared to ZELNORM administered alone. This increase in exposure is not considered clinically relevant.

Effect of Tegaserod on Other Drugs

No clinically significant effects of tegaserod on the pharmacokinetics of the following drugs were observed when used concomitantly with a single dose of ZELNORM 6 mg: theophylline (CYP1A2 substrate), dextromethorphan (CYP2D6 substrate), digoxin (P-gp substrate), warfarin (CYP2C9 substrate), or oral contraceptives (ethynyl estradiol and levonorgestrel).

Digoxin: Administration of a single dose of digoxin following ZELNORM 6 mg twice daily for 4 days reduced the mean Cmax and AUC of digoxin by approximately 15%. This reduction in digoxin exposure is not considered clinically relevant.

Warfarin: Coadministration of ZELNORM 6 mg twice daily with warfarin for seven days did not significantly alter the pharmacokinetics of either R- or S-warfarin or change the prothrombin time in healthy subjects.

Oral Contraceptives: Coadministration of ZELNORM 6 mg twice daily with 0.3 mg of ethinyl estradiol and 0.125 mg of levonorgestrel once daily did not affect the steady-state (Day 21) pharmacokinetics of ethinyl estradiol but reduced both the Cmax and AUC of levonorgestrel by 8%. This change in exposure is not considered clinically relevant.

In Vitro Studies Where the Drug Interaction Potential Was Not Further Evaluated Clinically

CYP enzymes

Tegaserod does not inhibit CYP2B6, CYP2C8, CYP2C9, CYP2C19, CYP2E1, and CYP3A4, and it does not induce CYP3A4 and CYP2B6.

Limited induction of CYP1A2 was observed at tegaserod concentrations in excess of 100 times the clinically relevant range.

M29 does not inhibit CYP1A2, CYP2B6, CYP2C8, CYP2C9, CYP2C19, CYP2D6, CYP2E1 and CYP3A4, and it does not induce CYP1A2, CYP2B6, or CYP3A4.

Transporters

Tegaserod is a substrate for BCRP and P-gp, but not a substrate of OAT1, OAT3, OCT1, OCT2, OATP1B1, OATP1B3, MATE1, MATE2-K or BSEP. Drug transporter data indicated a potential inhibition of MATE1, MATE2-K, and BCRP by tegaserod at high concentrations. However, at the clinical dose of ZELNORM, a significant in vivo drug interaction via inhibition of these transporters is unlikely.

M29 is a substrate of BCRP, P-gp, OAT3 and BSEP transporters, but not a substrate of OAT1, OCT1, OCT2, OATP1B1, OATP1B3, MATE1, and MATE2-K. M29 does not inhibit the following transporters: OAT1, OAT3, OCT1, OCT2, OATP1B1, OATP1B3, MATE1, MATE2-K, BCRP, P-gp, and BSEP.

13 NONCLINICAL TOXICOLOGY

13.1 Carcinogenesis, Mutagenesis, Impairment of Fertility

Tegaserod was not carcinogenic in rats given oral dietary doses up to 180 mg/kg/day (approximately 93 to 111 times the recommended dose based on AUC) for 110 to 124 weeks.

In mice, dietary administration of tegaserod for 104 weeks produced mucosal hyperplasia and adenocarcinoma of the small intestine at 600 mg/kg/day (approximately 83 to 110 times the recommended dose based on AUC). There was no evidence of carcinogenicity at lower doses (3 to 35 times the recommended dose based on AUC).

Tegaserod was not genotoxic in the in vitro Chinese hamster lung fibroblast (CHL/V79) cell chromosomal aberration and forward mutation test, the in vitro rat hepatocyte unscheduled DNA synthesis (UDS) test or the in vivo mouse micronucleus test. The results of the Ames test for mutagenicity were equivocal.

Tegaserod at oral (dietary) doses up to 240 mg/kg/day (approximately 57 times the recommended dose based on AUC) in male rats and 150 mg/kg/day (approximately 42 times the recommended dose based on AUC) in female rats was found to have no effect on fertility and reproductive performance.

13.2 Animal Toxicology and/or Pharmacology

Inhibition of the hERG (human Ether-a-go-go-Related Gene) channel was evident only in the micromolar concentration range with an IC50 of 13 micromolar (approximately 1300 times the Cmax in humans at the recommended dose). In in vitro studies, tegaserod had no effects on impulse conduction in isolated guinea pig papillary muscle at up to 100 times the Cmax in humans, Langendorff-perfused isolated rabbit heart (QT interval) at up to 1000 times the Cmax in humans, or human atrial myocytes at multiples up to 10 times the Cmax in humans. The major metabolite, M29, had no effect on QT in the Langendorff-perfused isolated rabbit heart at multiples up to 323 times the Cmax in humans.

In anesthetized and conscious dogs, tegaserod at doses up to 92 to 134 times the recommended dose based on Cmax did not alter heart rate, QRS interval duration, QTc or other ECG parameters. In chronic toxicology studies in rats and dogs, there were no treatment-related changes in cardiac morphology after tegaserod administration at doses up to 660 times the recommended dose based on AUC.

Although tegaserod is expected to bind to 5 HT2B receptors in humans at the recommended dose, there does not appear to be any potential for heart valve injury based on functional evidence of 5 HT2B receptor antagonism.

Studies with isolated coronary and mesenteric blood vessels from non-human primates and humans showed no vasoconstrictor effect at concentrations approximately 100 times the human Cmax. Tegaserod exhibited antagonism of 5 HT-mediated vasoconstriction via 5 HT1B receptors. In rat thoracic aortic rings that were pre-constricted with phenylephrine or norepinephrine, tegaserod produced vasorelaxation, with IC50 values 6 and 64 times the Cmax plasma concentrations in humans, respectively. No effects were observed in the basal tone of aortic rings at concentrations up to 1000 times the human Cmax.

In studies with an anesthetized rat model for measuring macro- and micro-circulation of the colon, intraduodenal dosing with tegaserod (approximately 7 times the recommended dose based on Cmax) produced no clinically relevant effect on blood pressure, heart rate, or vascular conductance.

14 CLINICAL STUDIES

Results in Women

ZELNORM is not recommended in females 65 years of age and older with IBS-C [see Indications and Dosage (1)].

In three multicenter, double-blind, placebo-controlled trials, 2,470 women (mean age 43 years [range 17 to 89 years]; 86% Caucasian, 10% African American) with at least a 3-month history of IBS-C symptoms prior to the baseline period that included abdominal pain, bloating and constipation received either ZELNORM 6 mg twice daily or placebo. In all patients, constipation was characterized by at least two of the following three symptoms each occurring >25% of the time over a 3-month period: <3 bowel movements/week, hard or lumpy stools, or straining with a bowel movement.

The design for the three trials consisted of a 4-week placebo-free baseline period followed by a 12-week double-blind treatment period. Studies 1 and 2 evaluated a fixed dose regimen of tegaserod 6 mg twice daily while Study 3 utilized a dose-titration design.

Each week of the 4-week placebo-free baseline period and the 12-week double-blind treatment period, patients were asked the question, “Please consider how you felt this past week in regard to your IBS, in particular your overall well-being, and symptoms of abdominal discomfort, pain and altered bowel habit. Compared to the way you usually felt before entering the trial, how would you rate your relief of symptoms during the past week?” The response variable consisted of the following five categories: completely relieved, considerably relieved, somewhat relieved, unchanged, or worse. Patients were classified as responders within a month if they were considerably or completely relieved for at least two of the four weeks, or if they were at least somewhat relieved for each of the four weeks.

Calculated response rates during month 1 and during month 3, as described above, are shown in Table 3. The differences in response rates vs. placebo were greater at month 1 than month 3.

Table 3. Efficacy Responder* Rates in the Three Placebo-Controlled IBS-C Trials
Study | Month 1 |  |  | Month 3**
 | Proportion of Responders (Female) |  |  | Proportion of Responders (Female)
 | ZELNORM 6 mg twice daily | Placebo | Difference [95% CI] | ZELNORM 6 mg twice daily | Placebo | Difference [95% CI]
1 | 76/244 | 42/240 | 14% | 95/244 | 66/240 | 11%
 | (31%) | (17%) | [6%,21%] | (39%) | (28%) | [3%,20%]
2 | 265/767 | 164/752 | 13% | 334/767 | 292/752 | 5%
 | (35%) | (22%) | [8%,17%] | (44%) | (39%) | [0%,10%]
3 | 80/233 | 47/234 | 14% | 100/233 | 88/234 | 5%
 | (34%) | (20%) | [6%,22%] | (43%) | (38%) | [-4%,14%]
*A responder is defined as a patient with ≥ 2 of 4 weeks with complete or considerable relief or 4 of 4 weeks with at least somewhat relief during the last 4 available weeks.
**Primary efficacy assessment.

In a subgroup of female patients less than 65 years of age (90%, 97%, and 91% of all female patients in Studies 1, 2 and 3, respectively), the treatment differences were generally similar at both month 1 and month 3 to the overall results shown in Table 3.

The same efficacy variable (i.e., complete relief, considerable relief, somewhat relief, unchanged, worse) was analyzed on a weekly basis. The proportion of all female patients with complete, considerable or somewhat relief at weeks 1, 4, 6, 8 and 12 are shown in Figure 1 below.

Figure 1: Weekly Proportion of Patients with Somewhat, Considerably and Complete Relief in the Three Placebo-Controlled IBS-C Trials

In addition, individual symptoms of abdominal pain/discomfort and bloating were assessed daily using a six or seven point intensity scale. A positive response was defined as at least a 1-point reduction in the scale. During the first four weeks in the fixed dose trials, 8% to 11% more ZELNORM-treated patients than placebo-treated patients were responders for abdominal pain/discomfort. Similarly, 9% to 12% more ZELNORM-treated patients were responders for bloating. Corresponding differences at month 3 were 1% to 10% responders for abdominal pain/discomfort and 4% to 11% responders for bloating. Patients on ZELNORM also experienced an increase in median number of bowel movements from 3.8/week at baseline to 6.3/week at month 1 and 6.0/week at month 3, while placebo patients increased from 4.0/week to 5.1/week at month 1 and 5.5/week at month 3.

Results in Men

In two randomized, placebo-controlled, double-blind trials enrolling 288 males, efficacy response rates were similar between ZELNORM and placebo in the male subgroup [see Indications and Usage (1)].

16 HOW SUPPLIED / STORAGE AND HANDLING

ZELNORM is supplied as 6 mg tegaserod whitish to slightly yellowish, round flat tablets with a beveled edge engraved with “ZEL” and “6”.

Unit Dose (blister pack)

- Box of 60 (strips of 10) NDC 0525-0971-60

Store at 25°C (77°F); excursions permitted to 15°C to 30°C (59°F to 86°F).

See USP Controlled Room Temperature. Protect from moisture.

17 PATIENT COUNSELING INFORMATION

Advise the patient to read the FDA-approved patient labeling (Medication Guide).

Cardiovascular Ischemic Events, Including MACE

Inform patients that stroke, myocardial infarction, and cardiovascular death have been reported in adults taking ZELNORM who had an increased risk of developing an adverse cardiovascular event based on their medical history. Advise patients to promptly seek medical attention if they develop symptoms of an MI, stroke, TIA, or angina. Also, advise patients to immediately inform their healthcare provider if they develop clinical or other evidence of cardiovascular ischemic heart disease (e.g., coronary artery disease) or other changes in their health status that could increase cardiovascular risk (e.g., smoking, hypertension, hyperlipidemia, diabetes mellitus, obesity) while taking ZELNORM [see Warnings and Precautions (5.1)].

Ischemic Colitis

Advise patients to stop taking ZELNORM and seek medical attention if they develop symptoms of ischemic colitis, such as rectal bleeding, bloody diarrhea or new or worsening abdominal pain [see Warnings and Precautions (5.2)].

Volume Depletion Associated with Diarrhea

Instruct patients to discontinue ZELNORM and contact their healthcare provider if they develop severe diarrhea, especially if they also experience symptoms of volume depletion (hypotension and/or syncope) [see Warnings and Precautions (5.3)].

Suicidal Ideation and Behavior

Counsel patients, their caregivers, and their families that ZELNORM may increase the risk of suicidal thoughts and behavior and advise them of the need to be alert for the emergence or worsening of symptoms of depression, any unusual changes in mood or behavior, or the emergence of suicidal thoughts, behavior, or thoughts of self-harm. Instruct patients, caregivers, and families that if any of these symptoms occur, they should immediately discontinue ZELNORM and report behaviors of concern to their healthcare provider [see Warnings and Precautions (5.4)].

Lactation

Advise a woman that breastfeeding is not recommended during treatment with ZELNORM [see Use in Specific Populations (8.2)].

Administration Information

Advise patients to take ZELNORM at least 30 minutes before a meal [see Dosage and Administration (2)].

Made in Germany

Distributed by:

Alfasigma USA, Inc.

Covington, LA 70433 USA

©2019. ZELNORM is a trademark of Alfasigma, USA Inc. All rights reserved.

PM-000413

Medication Guide
ZELNORMª (ZEL-norm)
(tegaserod) tablets, for oral use

What is the most important information I should know about ZELNORM?
ZELNORM can cause serious side effects, including:

- Major heart (cardiovascular) events. Major cardiovascular events such as stroke, heart attack, and death from stroke or heart attack have happened in adults taking ZELNORM who had an increased risk of having a cardiovascular event.

Risk factors that increase your risk of a major cardiovascular event include:

- currently smoke
- high blood pressure or your blood pressure is controlled with medicine that lowers your blood pressure
  high blood cholesterol levels or your blood cholesterol levels are controlled with medicine that lowers your blood cholesterol levels
- have or have had diabetes mellitus
- age 55 years or older
- obesity

Talk to your healthcare provider about risk factors you may have for a major cardiovascular event before you start taking ZELNORM.
Get emergency medical help right away if you have signs or symptoms of a heart attack, stroke, mini stroke (transient ischemic attack or TIA) or angina (chest pain that happens because your heart is not getting enough oxygen), including:
• chest pain that may spread to the arms, neck, jaw, back, or stomach area (abdomen)
• feeling sweaty
• shortness of breath
• feeling sick or vomiting
• sudden numbness or weakness, especially on one side of the body
• severe headache or confusion
• problems with vision, speech, or balance
Tell your healthcare provider right away if you are told that you have narrowing in the blood vessels that carry blood to your heart (coronary artery disease).

- Inflammation and injury of the intestines caused by reduced blood flow to the intestines (ischemic colitis). Ischemic colitis and other problems of the intestines caused by reduced blood flow to the intestines, that sometimes required hospitalization, have happened in some people taking ZELNORM. Stop taking ZELNORM and call your healthcare provider or get medical help if you have symptoms of ischemic colitis such as bleeding from your rectum, bloody diarrhea, or new or worsening stomach-area (abdominal) pain.
- Loss of body fluids caused by diarrhea. Diarrhea is a common side effect of ZELNORM, and it can sometimes be severe. Severe diarrhea can result in the loss of too much fluid from your body, low blood pressure, and fainting (loss of consciousness). Some people who had severe diarrhea during treatment with ZELNORM were hospitalized due to loss of too much body fluid. Stop taking ZELNORM and call your healthcare provider right away if you have severe diarrhea, especially if you also feel lightheaded, dizzy, or you faint.
- Suicidal thoughts and behavior. ZELNORM may increase the risk of suicidal thoughts and behavior. You, your caregiver, and your family should monitor you for changes in behavior. If you have any new or worsening symptoms of depression, unusual changes in mood or behavior, begin to have suicidal thoughts or behavior, or thoughts of self-harm, stop taking ZELNORM right away and tell your healthcare provider.

What is ZELNORM?
ZELNORM is a prescription medicine used for the treatment of adult women less than 65 years of age who have irritable bowel syndrome with constipation (IBS-C).
It is not known if ZELNORM is safe and effective in men with IBS-C.
It is not known if ZELNORM is safe and effective in children.

Do not take ZELNORM if you:

- have had a heart attack, stroke, transient ischemic attack or TIA, or angina.
- have had inflammation and injury of the intestines caused by reduced blood flow to the intestines (ischemic colitis).
- have severe kidney problems or end-stage kidney disease.
- have moderate or severe liver problems.
- have had an intestinal blockage (bowel obstruction), gallbladder problems that caused symptoms, or scar tissue that formed between the tissues of the abdomen and other organs in the abdomen.
- have or may have had a problem with the muscular valve that controls the flow of digestive juices (bile and pancreatic juice) to the first part of your intestine (sphincter of Oddi).
- are allergic to tegaserod.

Before taking ZELNORM, tell your healthcare provider about all of your medical conditions, including if you:

- currently smoke.
- have or have had high blood pressure or are taking medicine to lower your blood pressure.
- have or have had high blood cholesterol levels or are taking medicine to lower your blood cholesterol levels.
- have or have had diabetes.
- are having diarrhea or have diarrhea often.
- are pregnant or plan to become pregnant. It is not known if ZELNORM will harm your unborn baby.
- are breastfeeding or plan to breastfeed. It is not known if ZELNORM passes into your breast milk. You should not breastfeed if you take ZELNORM.

Tell your healthcare provider about all the medicines you take, including prescription and over-the-counter medicines, vitamins, and herbal supplements.

How should I take ZELNORM?

- Take ZELNORM exactly as your healthcare provider tells you to take it.
- The usual dose of ZELNORM is 1 tablet 2 times each day, taken by mouth.
- Take ZELNORM at least 30 minutes before a meal.
- If you take too much ZELNORM, call your healthcare provider or go to the nearest hospital emergency room right away.

What are the possible side effects of ZELNORM?
ZELNORM can cause serious side effects, including:

- See “What is the most important information I should know about ZELNORM?”

The most common side effects of ZELNORM are:
• headache
• stomach-area (abdominal) pain
• nausea
• gas
• indigestion
• dizziness
These are not all the possible side effects of ZELNORM.
Call your doctor for medical advice about side effects. You may report side effects to FDA at 1-800-FDA-1088.

How should I store ZELNORM?

- Store ZELNORM at room temperature between 68°F to 77°F (20°C to 25°C).
- Protect ZELNORM from moisture.

Keep ZELNORM and all medicines out of the reach of children.

General information about the safe and effective use of ZELNORM.
Medicines are sometimes prescribed for purposes other than those listed in a Medication Guide. Do not use ZELNORM for a condition for which it was not prescribed. Do not give ZELNORM to other people, even if they have the same symptoms that you have. It may harm them. You can ask your healthcare provider or pharmacist for information about ZELNORM that is written for health professionals.

What are the ingredients in ZELNORM?
Active ingredient: tegaserod
Inactive Ingredients: colloidal silicon dioxide, crospovidone, glyceryl behenate, hypromellose, and lactose monohydrate
Distributed by: Alfasigma USA, Inc., Covington, LA 70433 USA
©2019. ZELNORM is a trademark of Alfasigma, USA Inc. All rights reserved.
For more information, call 1‑855‑697‑9232.

This Medication Guide has been approved by the U.S. Food and Drug Administration. Revised: July 2019
PM-000413

PACKAGE LABEL

PRINCIPAL DISPLAY PANEL

NDC 0525-0971-30
Zelnorm
(tegaserod) tablets
6 mg per tablet
30 tablets (3 blister cards of 10 tablets each)

PACKAGE LABEL

PRINCIPAL DISPLAY PANEL

NDC 0525-0971-60
Zelnorm
(tegaserod) tablets
6 mg per tablet
60 tablets (6 blister cards of 10 tablets each)

PACKAGE LABEL

PRINCIPAL DISPLAY PANEL

NDC 0525-0971-10
Zelnorm
(tegaserod) tablets
6 mg per tablet
10 tablets (1 blister cards of 10 tablets each)